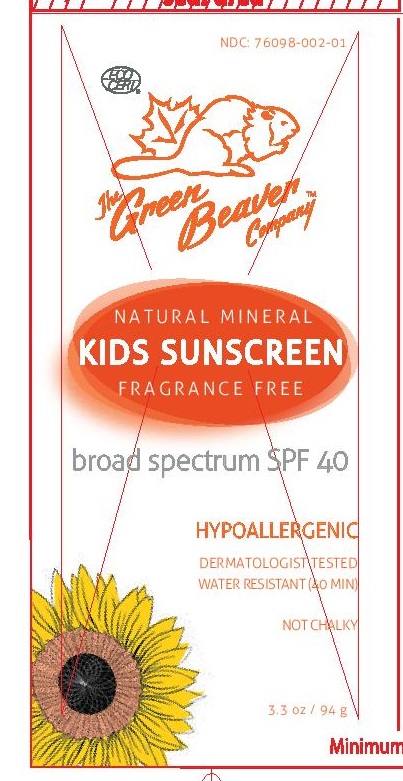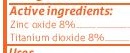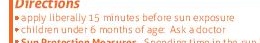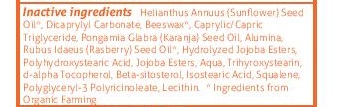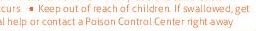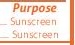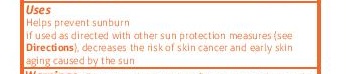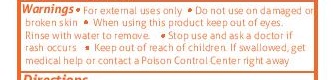 DRUG LABEL: The Green Beaver Company SPF 40 Kids Sunscreen
NDC: 76098-002 | Form: LOTION
Manufacturer: The Green Beaver Company
Category: otc | Type: HUMAN OTC DRUG LABEL
Date: 20210111

ACTIVE INGREDIENTS: ZINC OXIDE 8 g/100 g; TITANIUM DIOXIDE 8 g/100 g
INACTIVE INGREDIENTS: CEROTIC ACID; HYDROLYZED JOJOBA ESTERS (ACID FORM); SQUALENE; ALUMINUM OXIDE; POLYGLYCERYL-3 RICINOLEATE; TRIHYDROXYSTEARIN; .ALPHA.-TOCOPHEROL ACETATE, D-; SODIUM BETA-SITOSTERYL SULFATE; LECITHIN, SUNFLOWER; WATER; KARUM SEED OIL; HELIANTHUS ANNUUS SEED WAX; DICAPRYLYL CARBONATE; CAPRYLIC/CAPRIC/LAURIC TRIGLYCERIDE; RUBUS IDAEUS FRUIT VOLATILE OIL; POLYHYDROXYSTEARIC ACID (2300 MW); ISOSTEARIC ACID

The Green Beaver Kids Sunscreen SPF 40